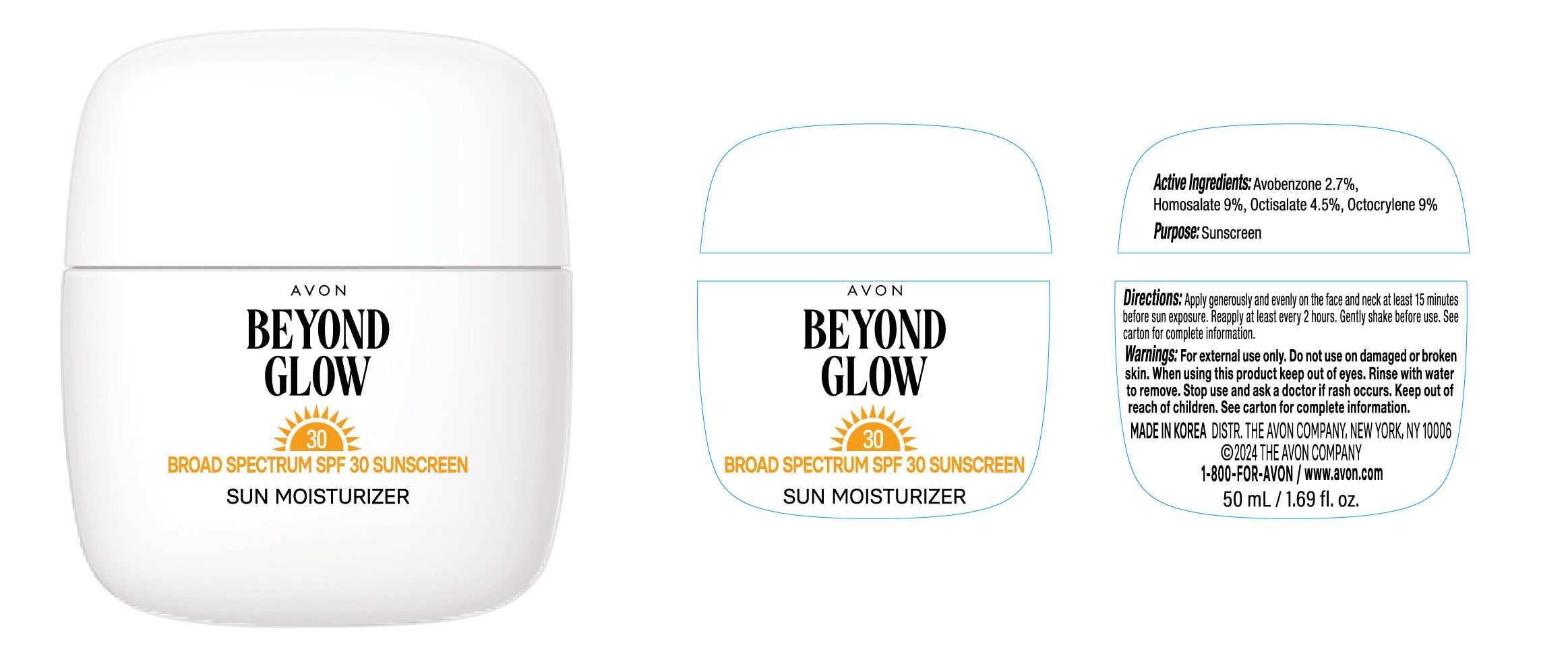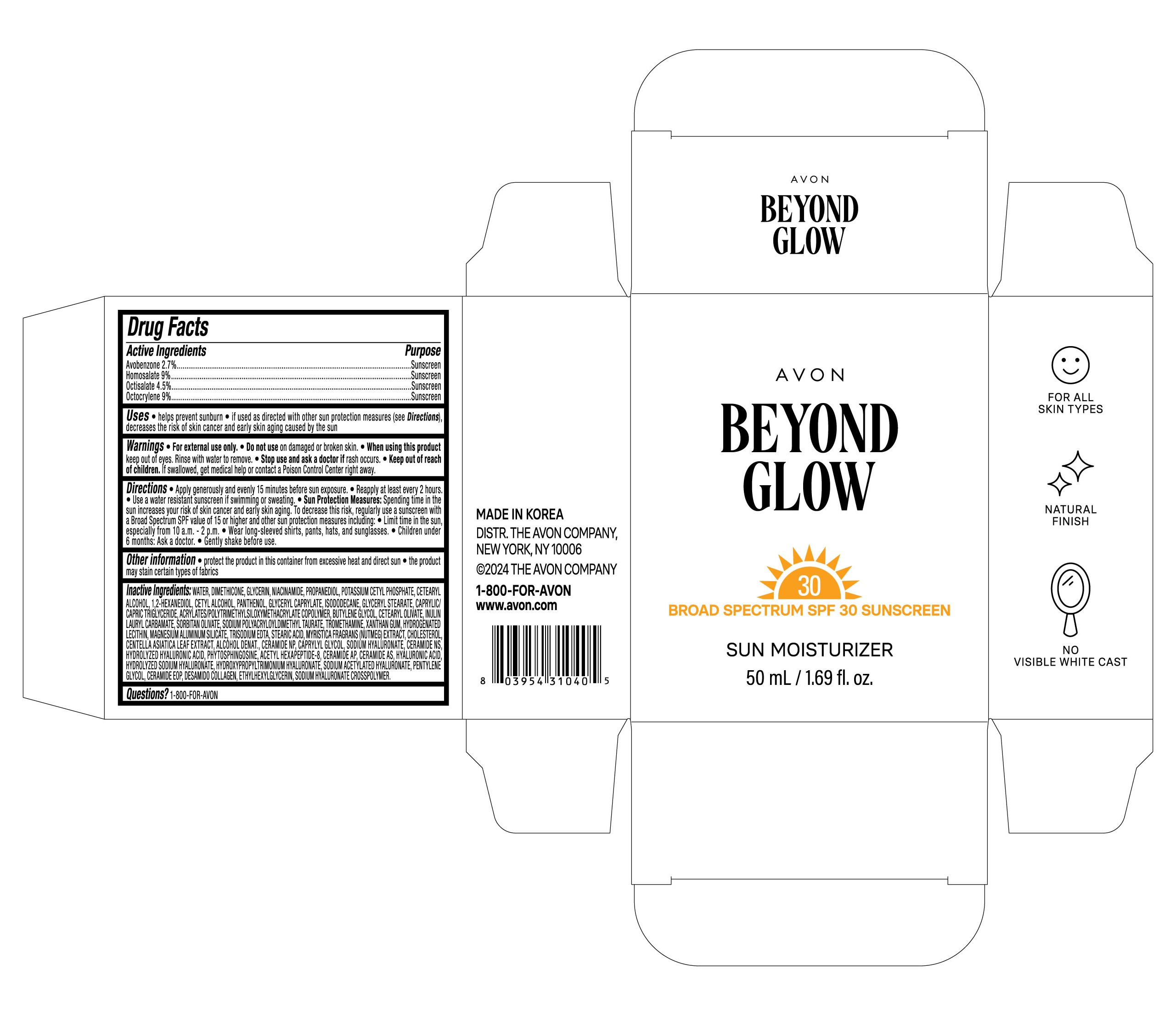 DRUG LABEL: AVON BEYOND GLOW SUN MOISTURIZER
NDC: 53208-422 | Form: CREAM
Manufacturer: LG HOUSEHOLD & HEALTH CARE LTD.
Category: otc | Type: HUMAN OTC DRUG LABEL
Date: 20250401

ACTIVE INGREDIENTS: AVOBENZONE 27 mg/1 mL; OCTISALATE 45 mg/1 mL; OCTOCRYLENE 90 mg/1 mL; HOMOSALATE 90 mg/1 mL
INACTIVE INGREDIENTS: 1,2-HEXANEDIOL; INULIN LAURYL CARBAMATE; XANTHAN GUM; CERAMIDE NS; PHYTOSPHINGOSINE; CERAMIDE AP; PENTYLENE GLYCOL; POTASSIUM CETYL PHOSPHATE; TRISODIUM EDTA; CERAMIDE NP; CETEARYL OLIVATE; CAPRYLYL GLYCOL; ACETYL HEXAPEPTIDE-8; PANTHENOL; ISODODECANE; GLYCERYL STEARATE; NUTMEG; WATER; CETYL ALCOHOL; DIMETHICONE; GLYCERYL CAPRYLATE; CETEARYL ALCOHOL; STEARIC ACID; CHOLESTEROL; SODIUM HYALURONATE; SODIUM ACETYLATED HYALURONATE; SODIUM POLYACRYLOYLDIMETHYL TAURATE; CENTELLA ASIATICA LEAF; ETHYLHEXYLGLYCERIN; CAPRYLIC/CAPRIC TRIGLYCERIDE; BUTYLENE GLYCOL; SORBITAN OLIVATE; NIACINAMIDE; PROPANEDIOL; HYALURONIC ACID; GLYCERIN; DEHYDRATED ALCOHOL; TROMETHAMINE; MAGNESIUM ALUMINUM SILICATE; PEG-9 DIGLYCIDYL ETHER/SODIUM HYALURONATE CROSSPOLYMER; BUTYL ACRYLATE/METHYL METHACRYLATE/TRIMETHYLSILOXYMETHACRYLATE COPOLYMER; CERAMIDE 4; HYDROGENATED SOYBEAN LECITHIN

Active Ingredients

Avobenzone 2.7%

Homosalate 9%

Octisalate 4.5%

Octocrylene 9%

Purpose

Sunscreen

Uses

- helps prevent sunburn
- if used as directed with other sun protection measures (see Directions), decreases the risk of skin cancer and early skin aging caused by the sun

Warnings

For external use only.

Do not use on damaged or broken skin.

When using this product keep out of eyes. Rinse with water to remove.

Stop use and ask a doctor if rash occurs.

Keep out of reach of children.

DOSAGE AND ADMINISTRATION

If swallowed, get medical help or contact a Poison Control Center right away.

Directions

- Apply generously and evenly 15 minutes before sun exposure.
- Reapply at least every 2 hours.
- Use a water resistant sunscreen if swimming or sweating.
- Sun Protection Measures: Spending time in the sun increases your risk of skin cancer and early skin aging. To decrease this risk, regularly use a sunscreen with a Broad Spectrum SPF value of 15 or higher and other sun protection measures including:
- Limit time in the sun, especially from 10 a.m. - 2 p.m.
- Wear long-sleeved shirts, pants, hats, and sunglasses.
- Children under 6 months: Ask a doctor.
- Gently shake before use.

Other information

- protect the product in this container from excessive heat and direct sun
- the product may stain certain types of fabrics

Inactive Ingredients

WATER, DIMETHICONE, GLYCERIN, NIACINAMIDE, PROPANEDIOL, POTASSIUM CETYL PHOSPHATE, CETEARYL ALCOHOL, 1,2-HEXANEDIOL, CETYL ALCOHOL, PANTHENOL, GLYCERYL CAPRYLATE, ISODODECANE, GLYCERYL STEARATE, CAPRYLIC/CAPRIC TRIGLYCERIDE, ACRYLATES/POLYTRIMETHYLSILOXYMETHACRYLATE COPOLYMER, BUTYLENE GLYCOL, CETEARYL OLIVATE, INULIN LAURYL CARBAMATE, SORBITAN OLIVATE, SODIUM POLYACRYLOYLDIMETHYL TAURATE, TROMETHAMINE, XANTHAN GUM, HYDROGENATED LECITHIN, MAGNESIUM ALUMINUM SILICATE, TRISODIUM EDTA, STEARIC ACID, MYRISTICA FRAGRANS (NUTMEG) EXTRACT, CHOLESTEROL, CENTELLA ASIATICA LEAF EXTRACT, ALCOHOL DENAT., CERAMIDE NP, CAPRYLYL GLYCOL, SODIUM HYALURONATE, CERAMIDE NS, HYDROLYZED HYALURONIC ACID, PHYTOSPHINGOSINE, ACETYL HEXAPEPTIDE-8, CERAMIDE AP, CERAMIDE AS, HYALURONIC ACID, HYDROLYZED SODIUM HYALURONATE, HYDROXYPROPYLTRIMONIUM HYALURONATE, SODIUM ACETYLATED HYALURONATE, PENTYLENE GLYCOL, CERAMIDE EOP, DESAMIDO COLLAGEN, ETHYLHEXYLGLYCERIN, SODIUM HYALURONATE CROSSPOLYMER.

Questions?

1-800-FOR-AVON